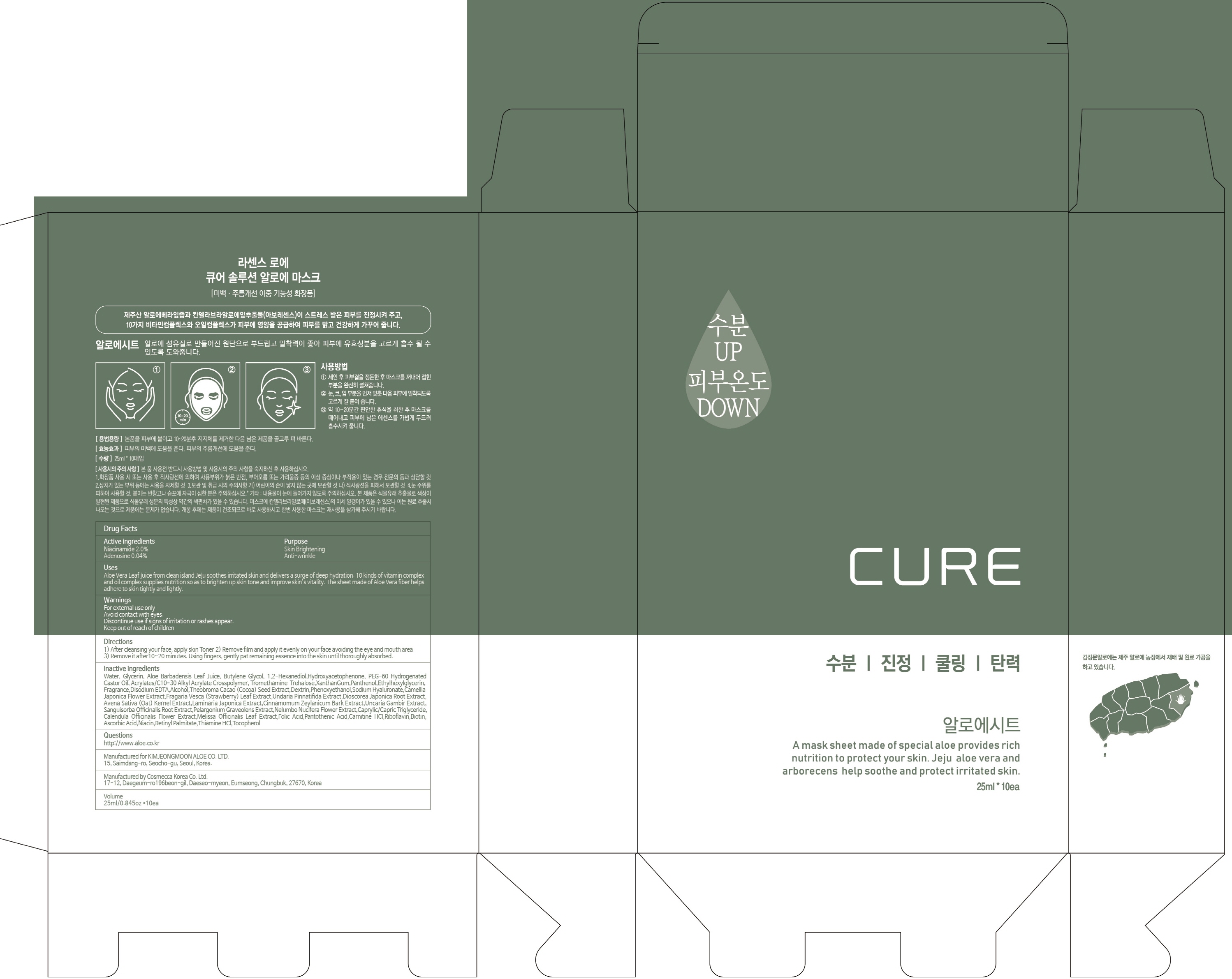 DRUG LABEL: Ra Sence Loe Cure Solu tion Aloe Mask
NDC: 50410-100 | Form: PATCH
Manufacturer: Kimjeongmoon Aloe Co., Ltd.
Category: otc | Type: HUMAN OTC DRUG LABEL
Date: 20181002

ACTIVE INGREDIENTS: Niacinamide 0.5 g/25 mL; Adenosine 0.01 g/25 mL
INACTIVE INGREDIENTS: Water; Glycerin

ACTIVE INGREDIENT

Active Ingredient: Niacinamide 2.0%, Adenosine 0.04%

INACTIVE INGREDIENT

Inactive ingredients:

Water, Glycerin, Aloe Barbadensis Leaf Juice, Butylene Glycol, 1,2-Hexanediol,Hydroxyacetophenone, PEG-60 Hydrogenated Castor Oil,
Acrylates/C10-30 Alkyl Acrylate Crosspolymer, Tromethamine Trehalose
,XanthanGum,Panthenol,Ethylhexylglycerin,Fragrance,Disodium EDTA,Alcohol,Theobroma Cacao (Cocoa) Seed Extract,,Dextrin,Phenoxyethanol,Sodium Hyaluronate,Camellia Japonica Flower Extract,Fragaria Vesca (Strawberry) Leaf Extract,Undaria Pinnatifida Extract,Dioscorea Japonica Root Extract,Avena Sativa (Oat) Kernel Extract,Laminaria Japonica Extract,Cinnamomum Zeylanicum Bark Extract,Uncaria Gambir Extract,Sanguisorba Officinalis Root Extract,Pelargonium Graveolens Extract,Nelumbo Nucifera Flower Extract,Caprylic/Capric Triglyceride,Calendula Officinalis Flower Extract,Melissa Officinalis Leaf Extract,Folic Acid,Pantothenic Acid,Carnitine HCl,Riboflavin,Biotin,Ascorbic Acid,Niacin,Retinyl Palmitate,Thiamine HCl,Tocopherol

PURPOSE

Purpose: Skin Brightening, Anti-wrinkle

WARNINGS

For external use only
Avoid contact with eyes.
Discontinue use if signs of irritation or rashes appear.
Keep out of reach of children

KEEP OUT OF REACH OF CHILDREN

Uses

Aloe Vera Leaf juice from clean island Jeju soothes irritated skin and delivers a surge of deep hydration. 10 kinds of vitamin complex and oil complex supplies nutrition so as to brighten up skin tone and improve skin’s vitality. The sheet made of Aloe Vera fiber helps adhere to skin tightly and lightly.

Directions

1) After cleansing your face, apply skin Toner.2) Remove film and apply it evenly on your face avoiding the eye and mouth area. 3) Remove it after10~20 minutes. Using fingers, gently pat remaining essence into the skin until thoroughly absorbed.